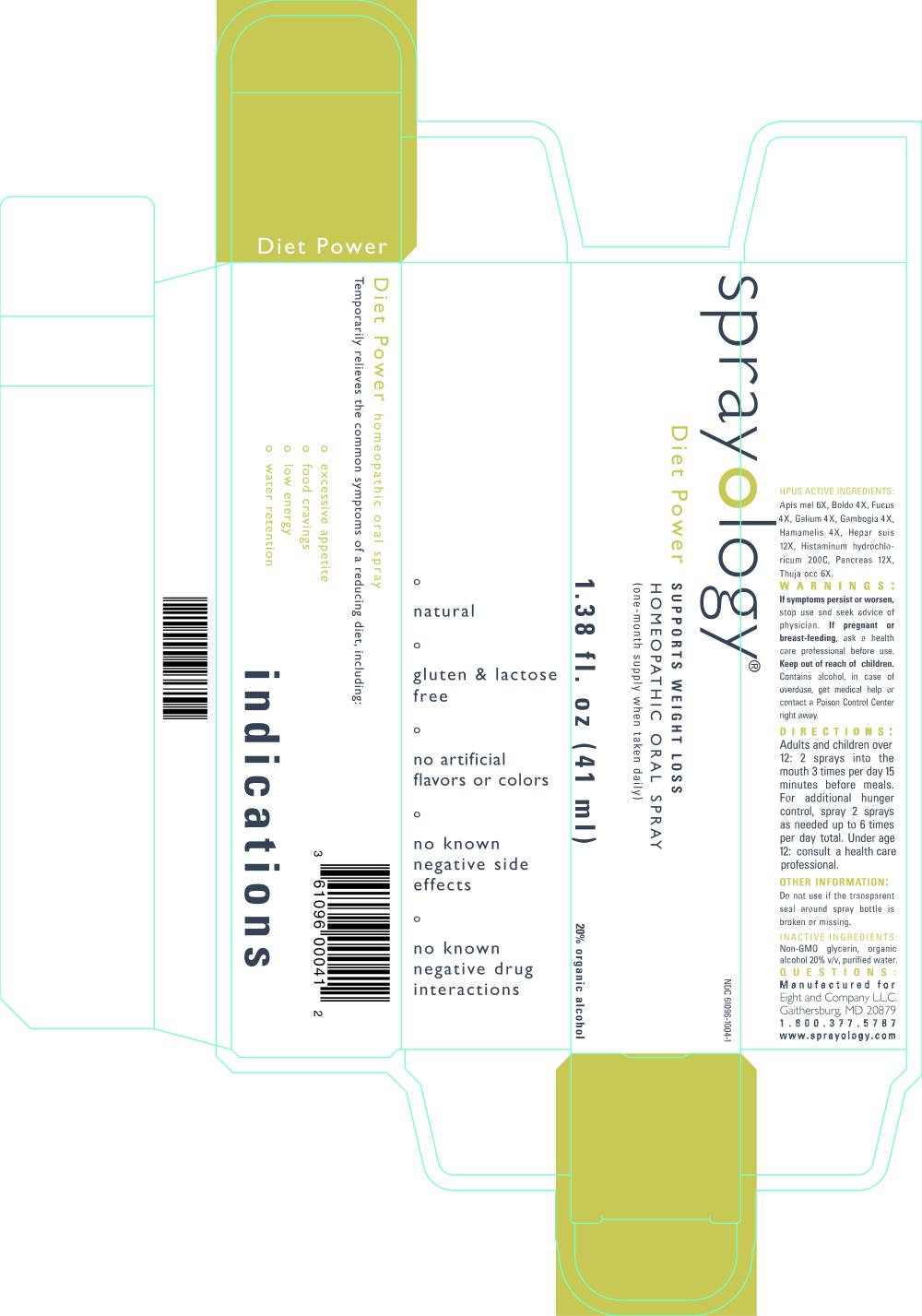 DRUG LABEL: Diet Power
NDC: 61096-1004 | Form: LIQUID
Manufacturer: Eight and Company L.L.C
Category: homeopathic | Type: HUMAN OTC DRUG LABEL
Date: 20190424

ACTIVE INGREDIENTS: APIS MELLIFERA 6 [hp_X]/41 mL; PEUMUS BOLDUS LEAF 4 [hp_X]/41 mL; FUCUS VESICULOSUS 4 [hp_X]/41 mL; GALIUM APARINE 4 [hp_X]/41 mL; GAMBOGE 4 [hp_X]/41 mL; HAMAMELIS VIRGINIANA ROOT BARK/STEM BARK 4 [hp_X]/41 mL; PORK LIVER 12 [hp_X]/41 mL; HISTAMINE DIHYDROCHLORIDE 200 [hp_C]/41 mL; SUS SCROFA PANCREAS 12 [hp_X]/41 mL; THUJA OCCIDENTALIS LEAFY TWIG 6 [hp_X]/41 mL
INACTIVE INGREDIENTS: GLYCERIN; ALCOHOL; WATER

Diet Power

ACTIVE INGREDIENT

Active Ingredients: Apis mel 6X, Boldo 4X, Fucus 4X, Galium 4X, Gambogia 4X, Hamamelis 4X, Hepar suis 12X, Histaminum hydrochloricum 200C, Pancreas 12X, Thuja occ 6X.

WARNINGS

Warnings: If symptoms persist or worsen, stop use and seek advice of physician. If pregnant or breast-feeding, ask a health care professional before use. Keep out of reach of children. Contains alcohol, in case of overdose, get medical help or contact a Poison Control Center right away.

Keep out of reach of children.

Directions:

- Adults and children over 12: 2 sprays into the mouth 3 times per day 15 minutes before meals. For additional hunger control, spray 2 sprays as needed up to 6 times per day total.
- Under age 12: consult a health care professional.

PURPOSE

Temporarily relieves the common symptoms of a reducing diet, including:

- excessive appetite
- food cravings
- low energy
- water retention

Other Information: Do not use if the transparent seal around spray bottle is broken or missing.

INACTIVE INGREDIENT

Inactive Ingredients: Non-GMO glycerin v/v, organic alcohol 20% v/v and purified water.

INDICATIONS AND USAGE

Temporarily relieves the common symptoms of a reducing diet, including:

° excessive appetite

° food cravings

° low energy

° water retention

° natural

° gluten & lactose free

° no artificial flavors or colors

° no known negative side effects

° no known negative drug interactions